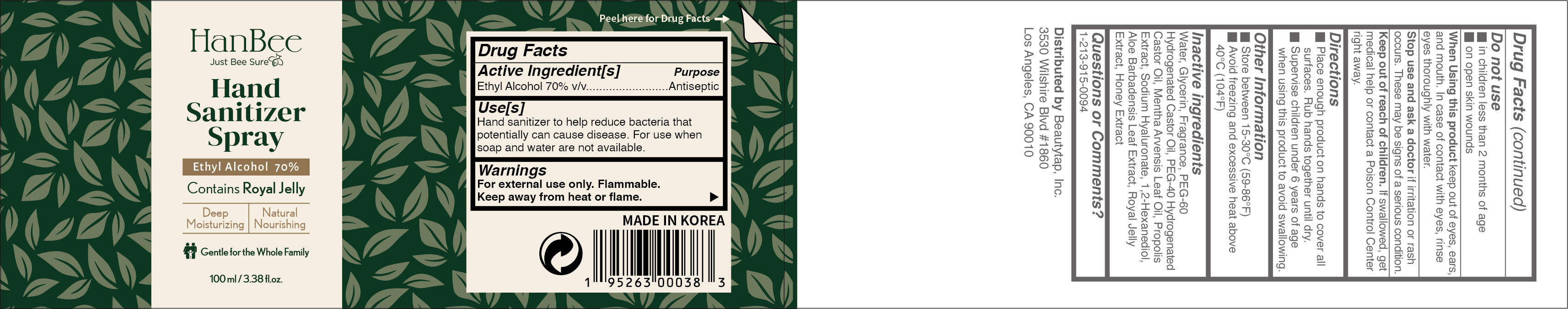 DRUG LABEL: HanBee Hand Sanitizer 70% 100ml
NDC: 73862-225 | Form: SPRAY
Manufacturer: E.CIS Cosmetic Co.,Ltd
Category: otc | Type: HUMAN OTC DRUG LABEL
Date: 20210309

ACTIVE INGREDIENTS: ALCOHOL 70 mL/100 mL
INACTIVE INGREDIENTS: ALOE VERA LEAF; PROPOLIS WAX; GLYCERIN; 1,2-HEXANEDIOL; WATER; HYALURONATE SODIUM; ROYAL JELLY; PEG-60 HYDROGENATED CASTOR OIL; HONEY; POLYOXYL 40 HYDROGENATED CASTOR OIL; MENTHA ARVENSIS LEAF OIL

HanBee Hand Sanitizer Spray 70% 100ml

Active Ingredient(s)

Alcohol 70% v/v. Purpose: Antiseptic

Purpose

Antiseptic, Hand Sanitizer

Use

Hand sanitizer to help reduce bacteria that potentially can cause disease. For use when soap and water are not available.

Warnings

For external use only. Flammable. Keep away from heat or flame

Do not use

- in children less than 2 months of age
- on open skin wounds

When using this product keep out of eyes, ears, and mouth. In case of contact with eyes, rinse eyes thoroughly with water.
Stop use and ask a doctor if irritation or rash occurs. These may be signs of a serious condition.
Keep out of reach of children. If swallowed, get medical help or contact a Poison Control Center right away.

Stop use and ask a doctor if irritation or rash occurs. These may be signs of a serious condition.

Keep out of reach of children. If swallowed, get medical help or contact a Poison Control Center right away.

Directions

- Place enough product on hands to cover all surfaces. Rub hands together until dry.
- Supervise children under 6 years of age when using this product to avoid swallowing.

Other information

- Store between 15-30C (59-86F)
- Avoid freezing and excessive heat above 40C (104F)

Inactive ingredients

Water, Glycerin, Fragrance, PEG-60 Hydrogenated Castor Oil, PEG-40 Hydrogenated Castor Oil, Mentha Arvensis Leaf Oil, Propolis Extract, Sodium Hyaluronate, 1,2-Hexanediol, Aloe Barbadensis Leaf Extract, Royal Jelly Extract, Honey Extract

Package Label - Principal Display Panel

HanBee
Just Bee Sure
Hand Sanitizer Spray
Ethyl Alcohol 70%
Contains Royal Jelly
Deep Moisturizing Natural Nourishing
Gentle for the Whole Family
100 mL (3.38 fl. oz.)